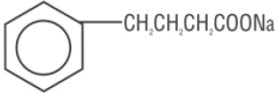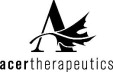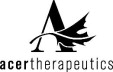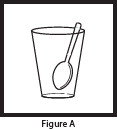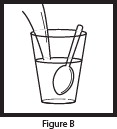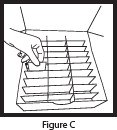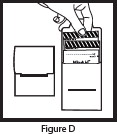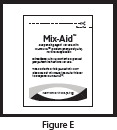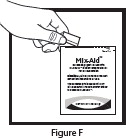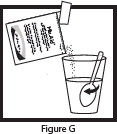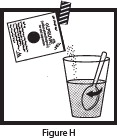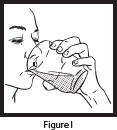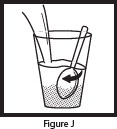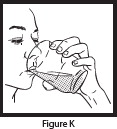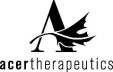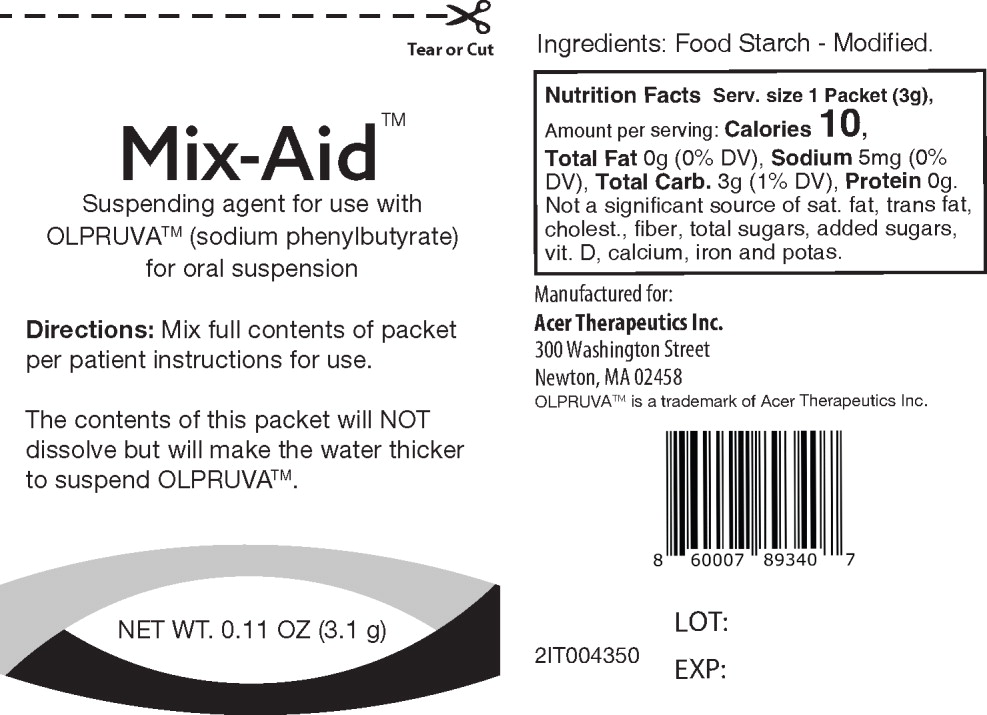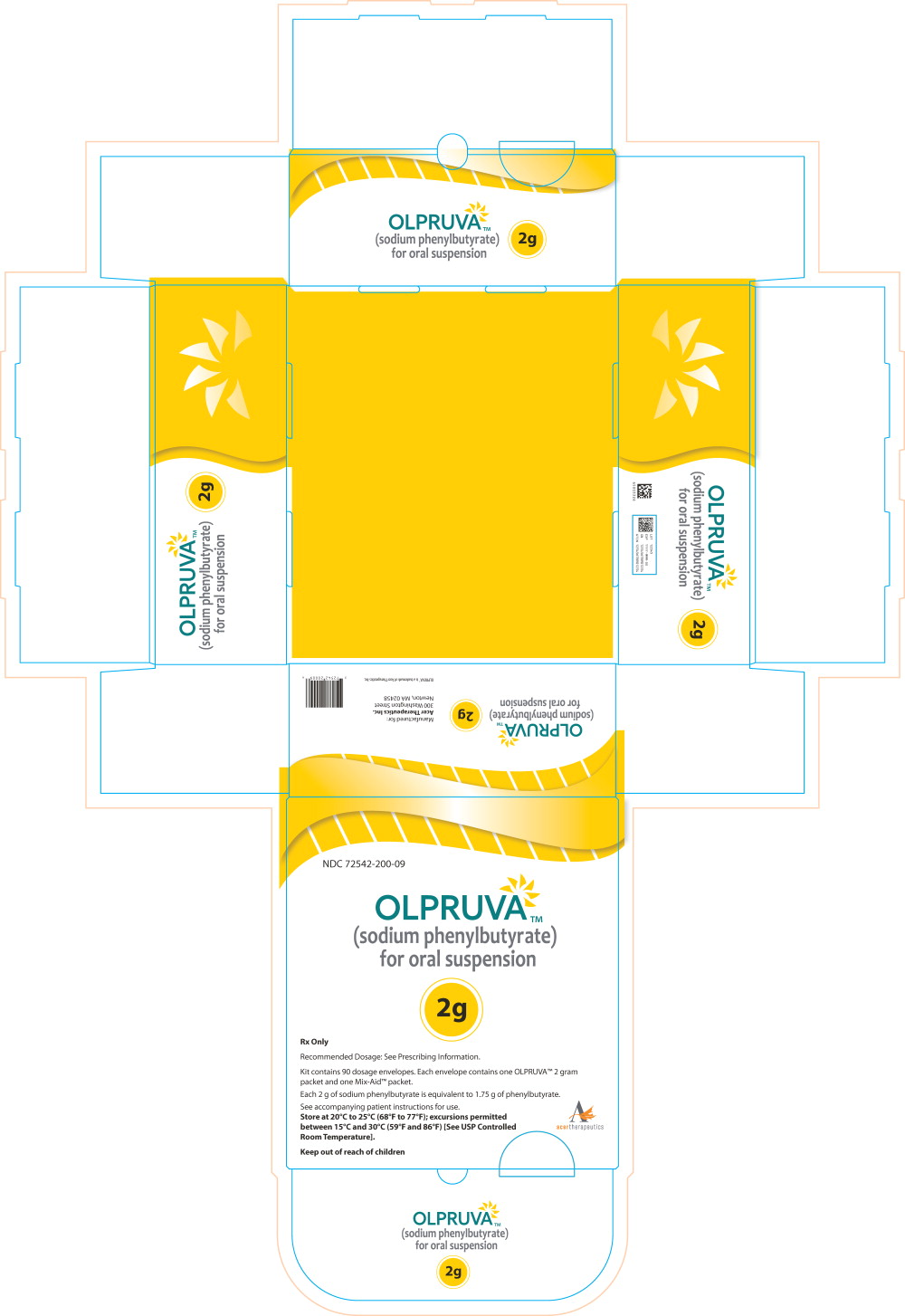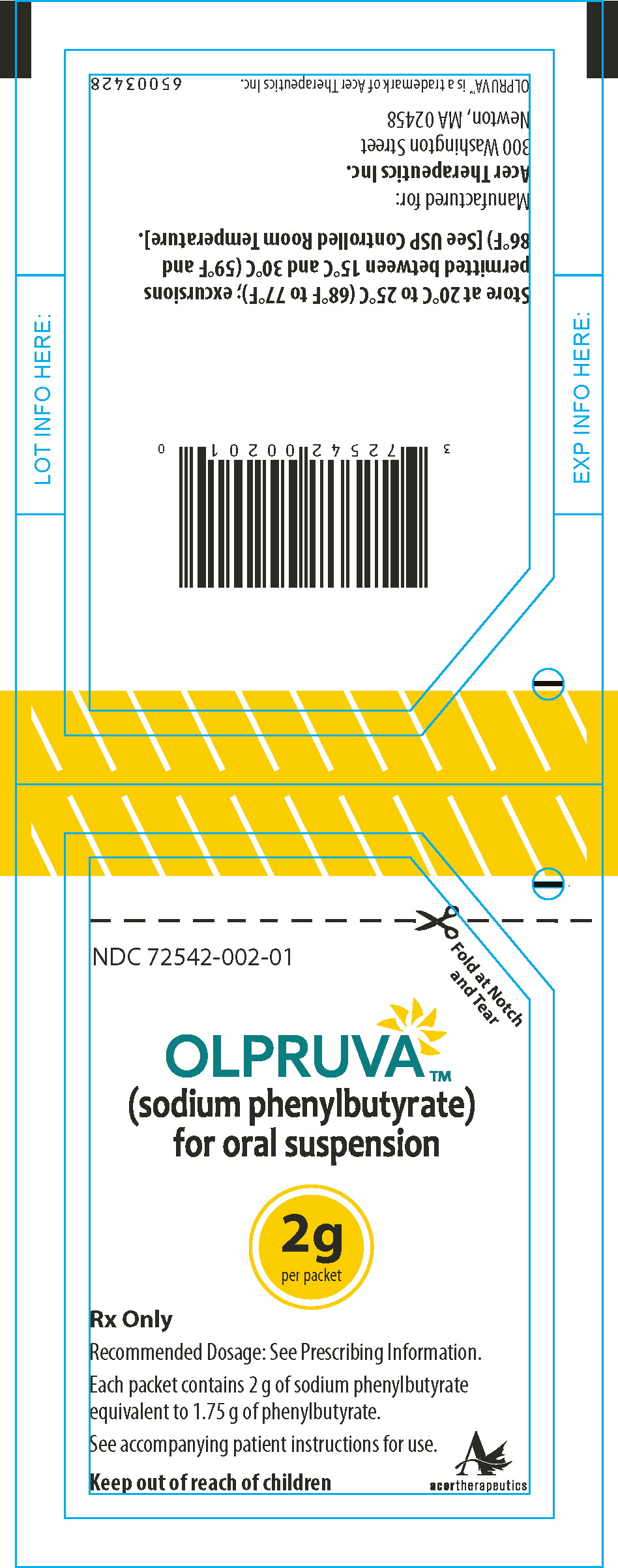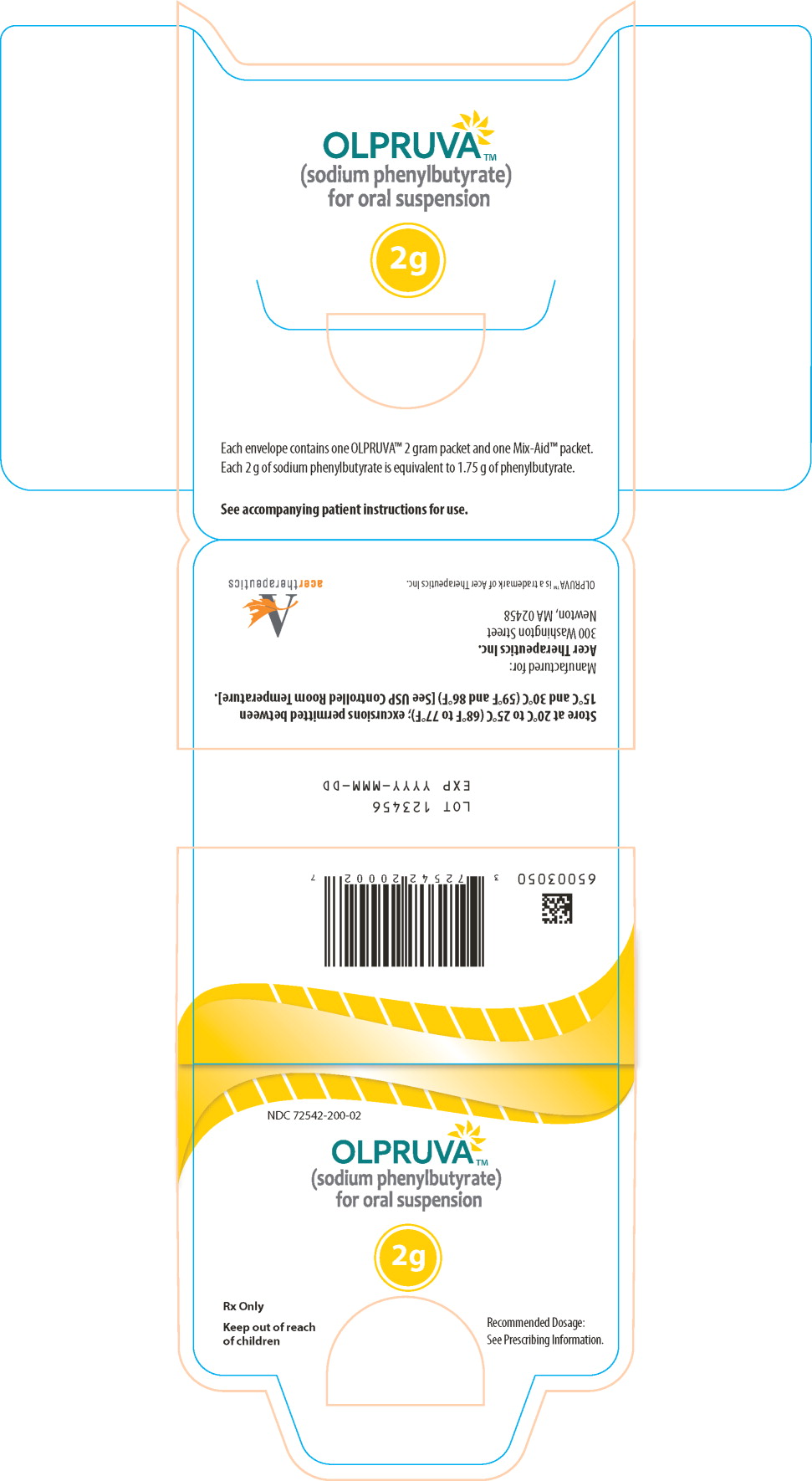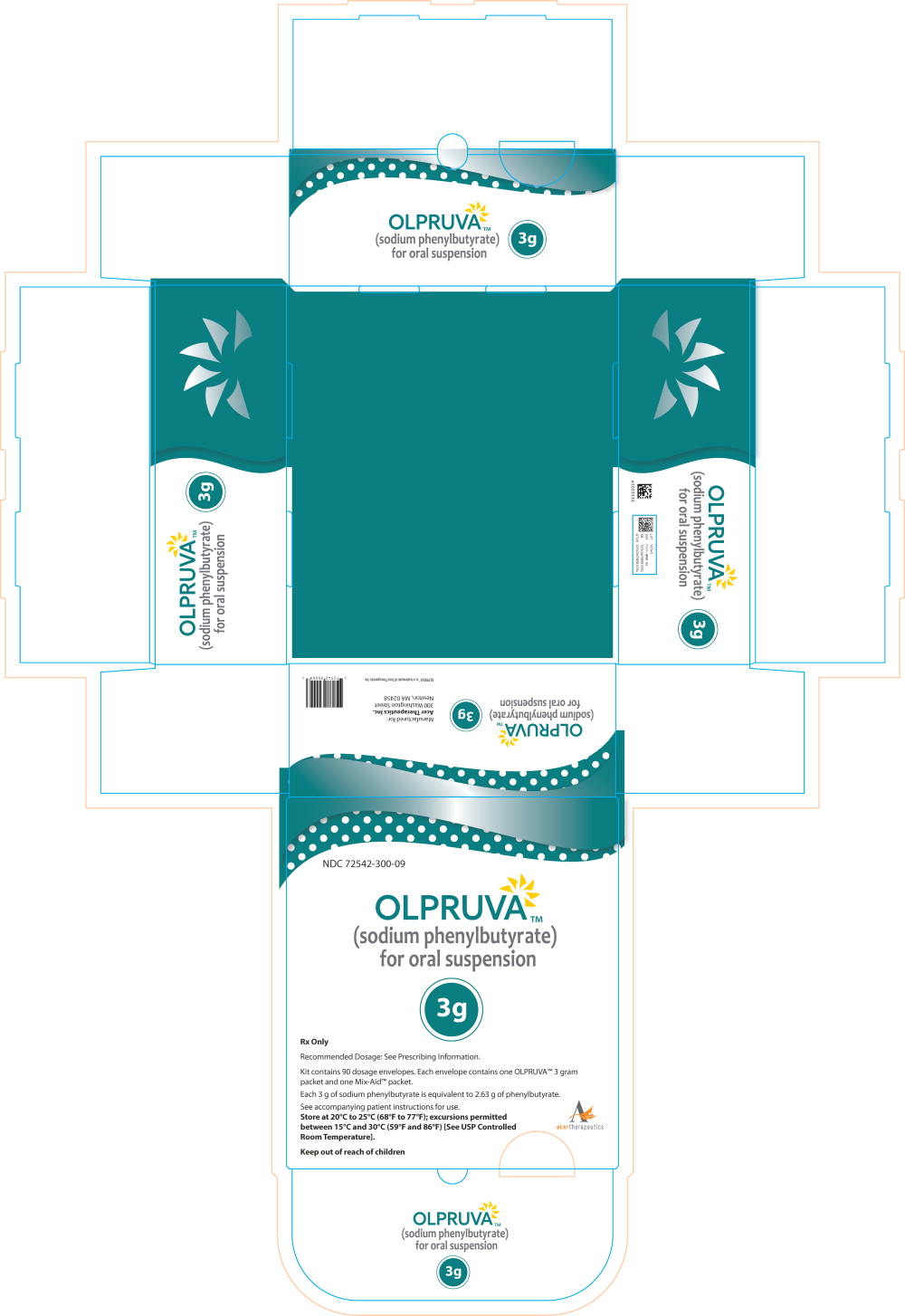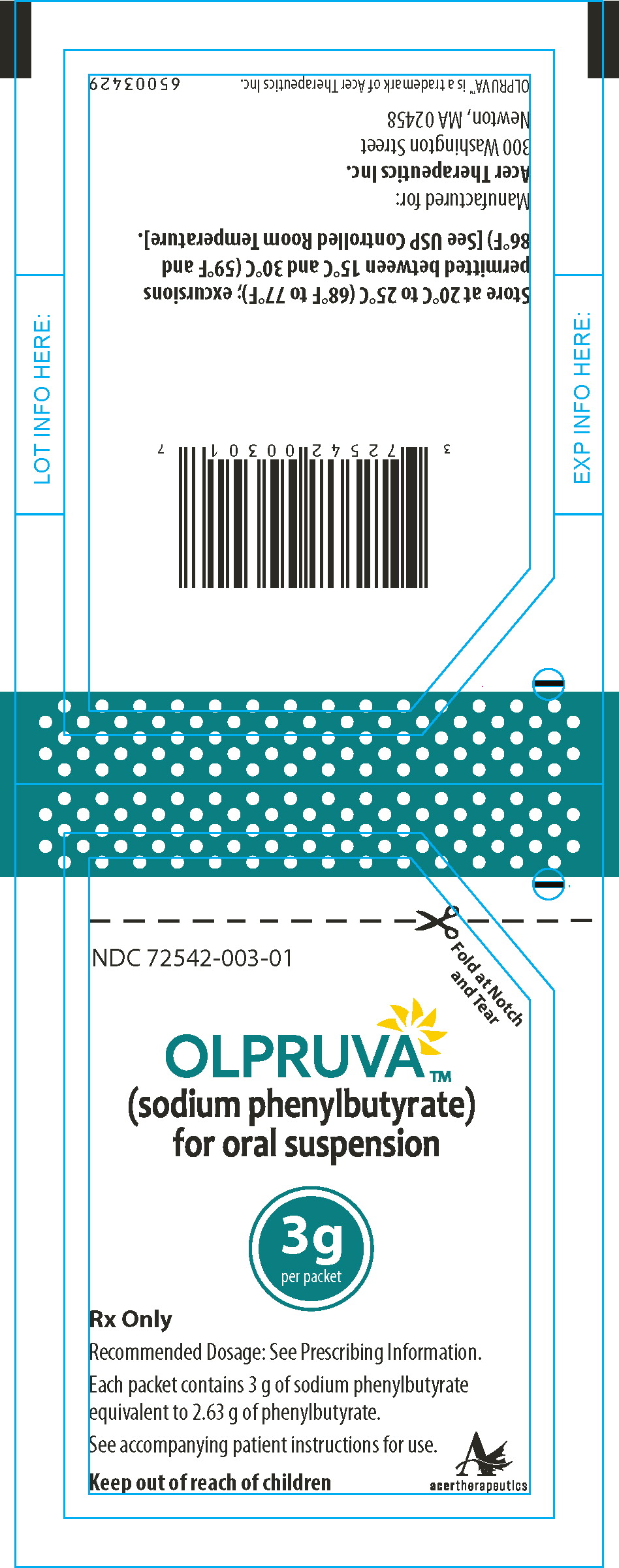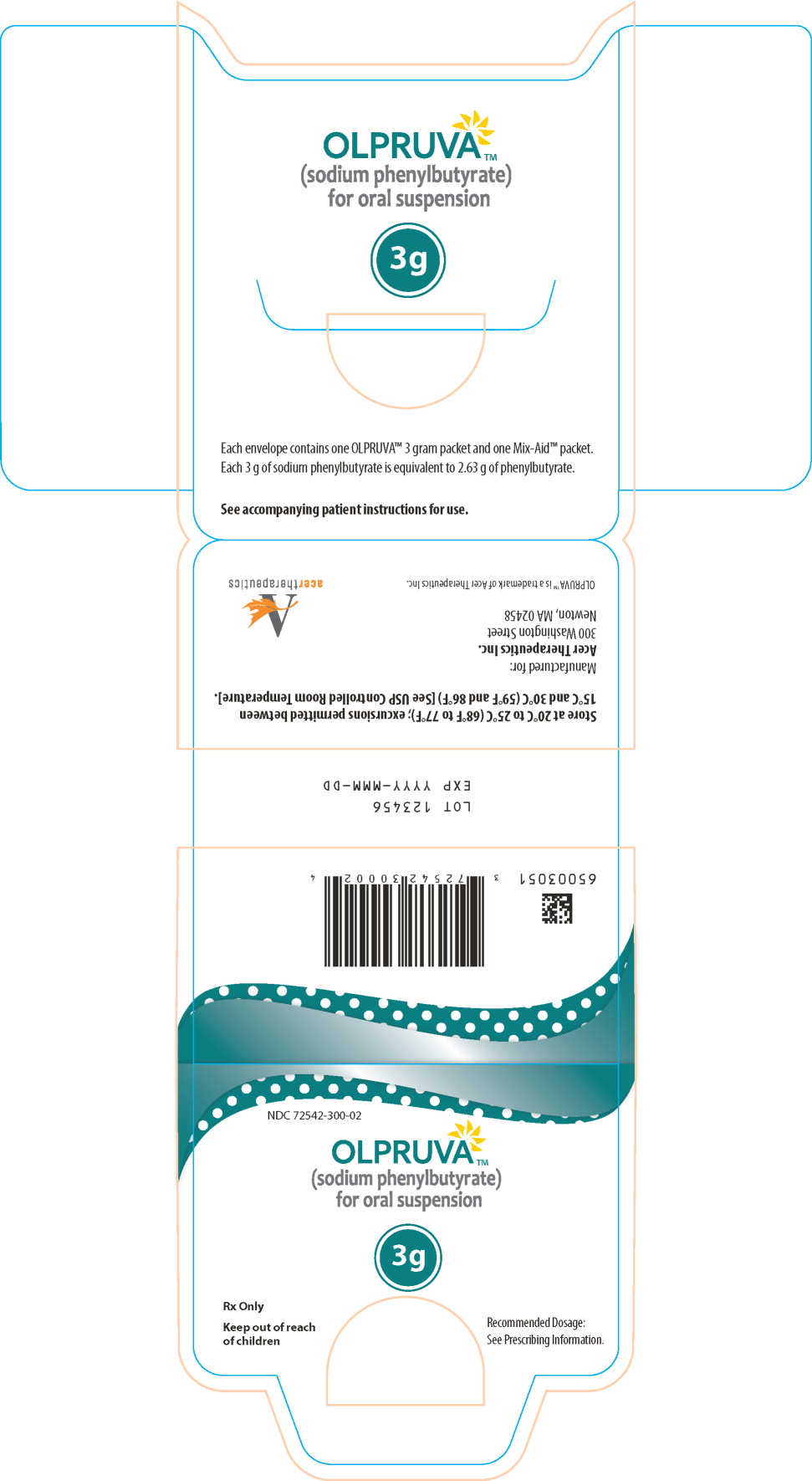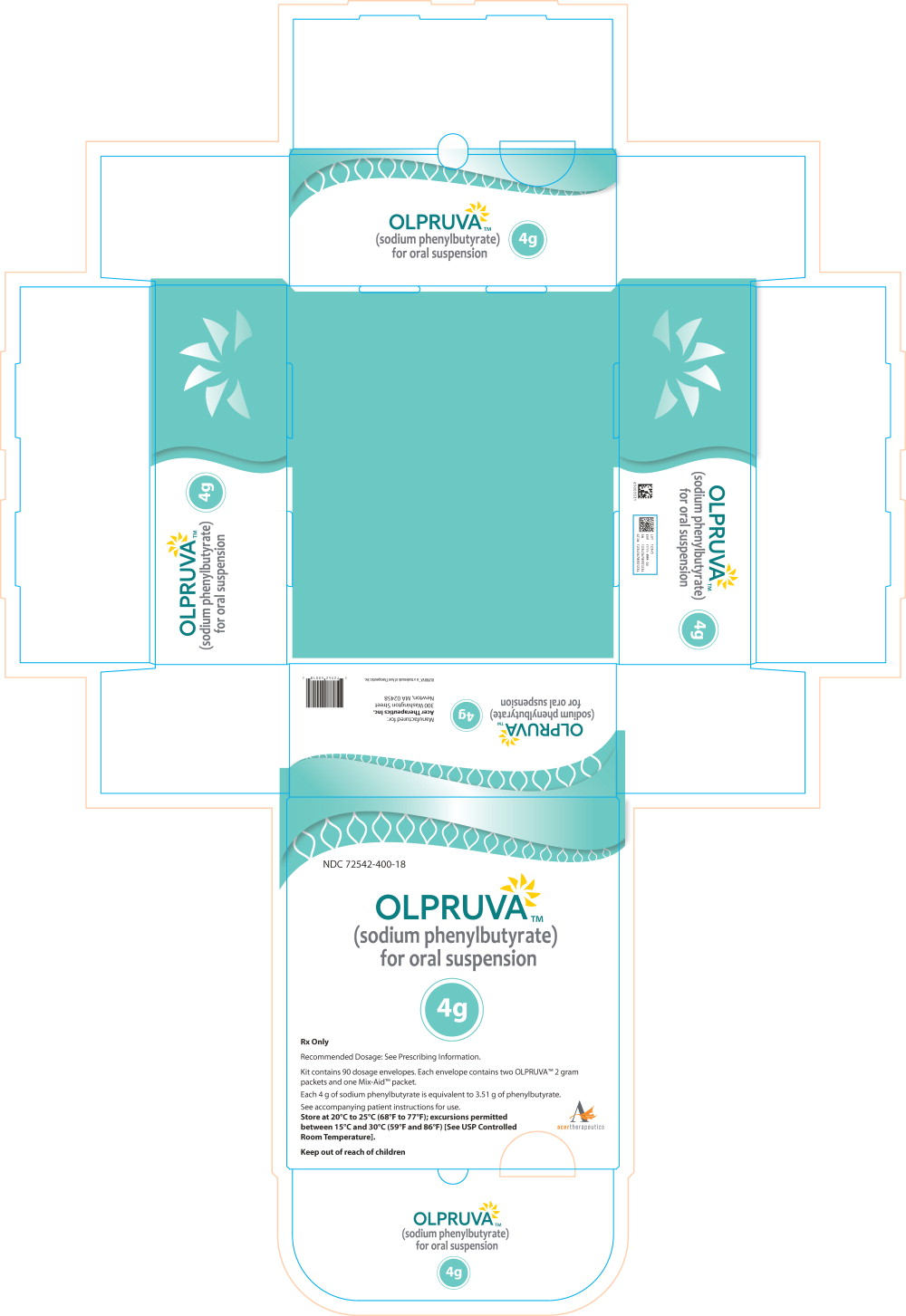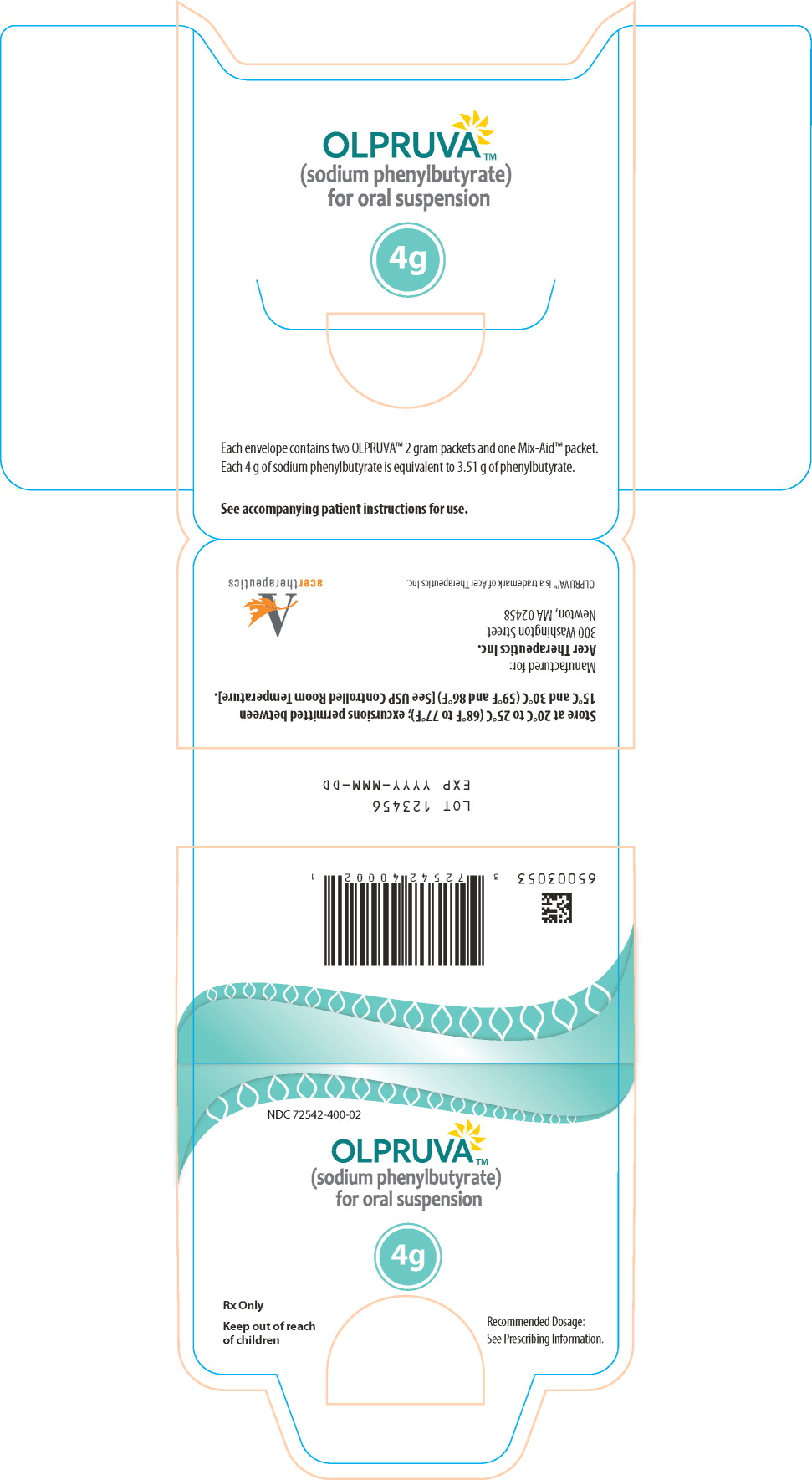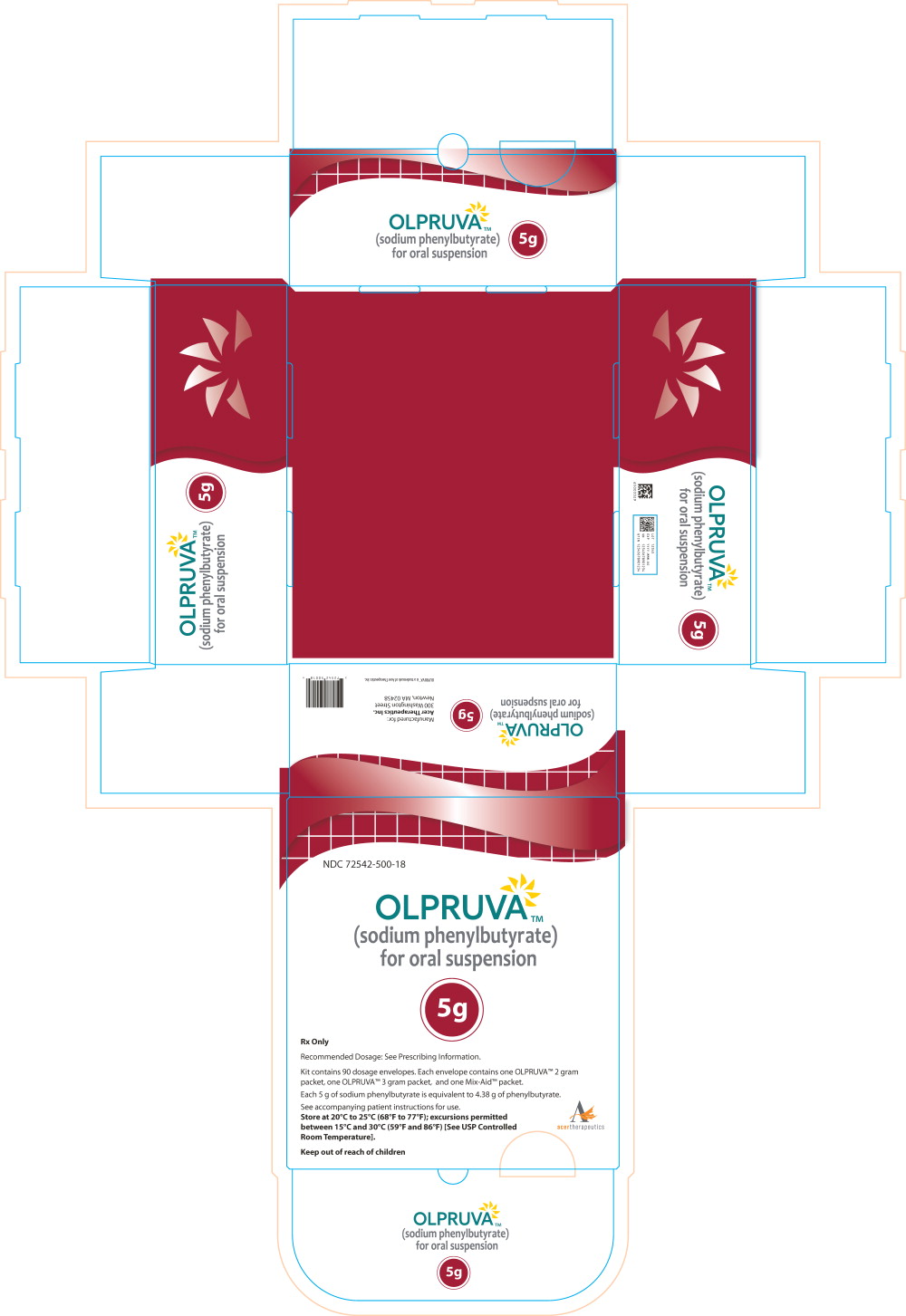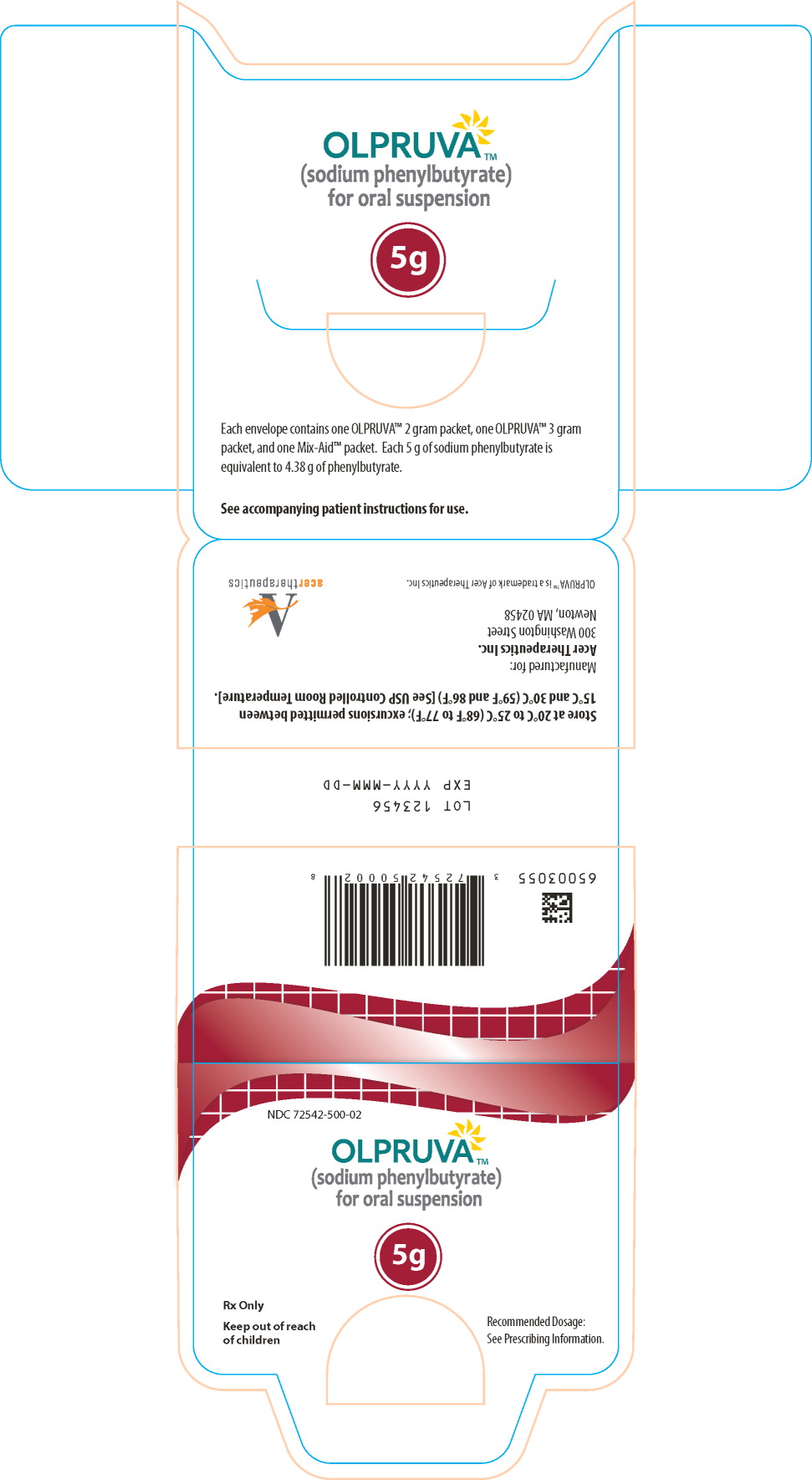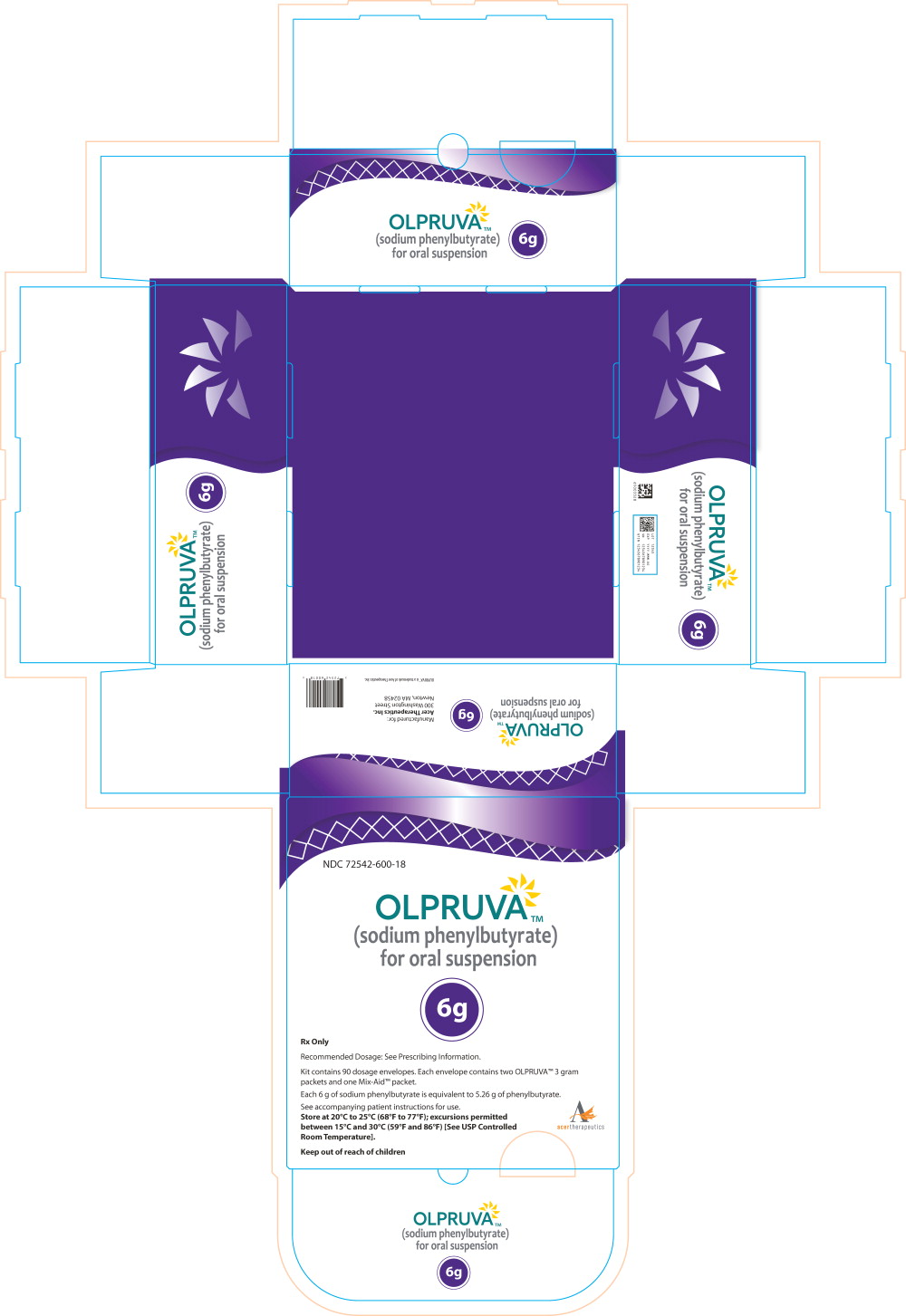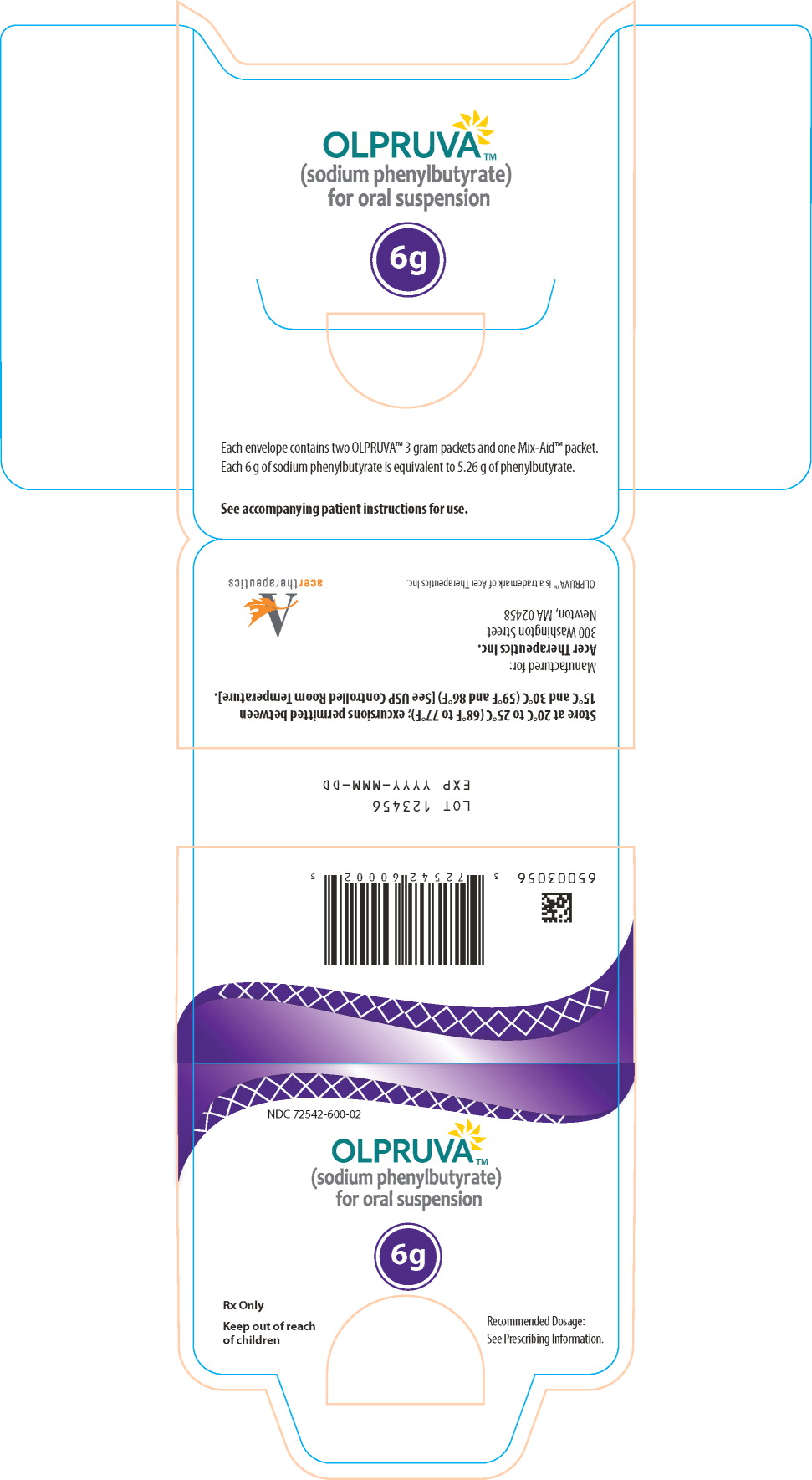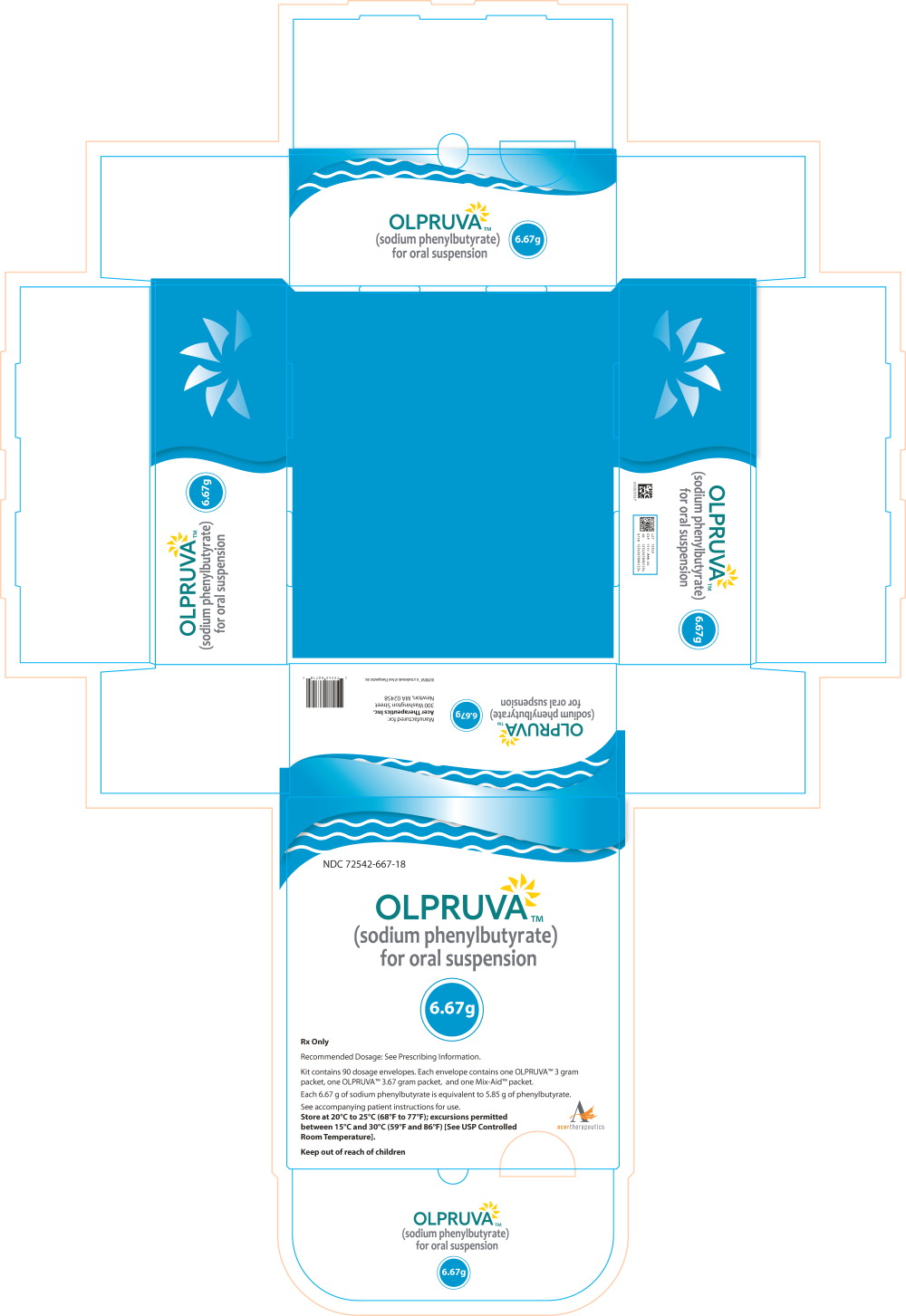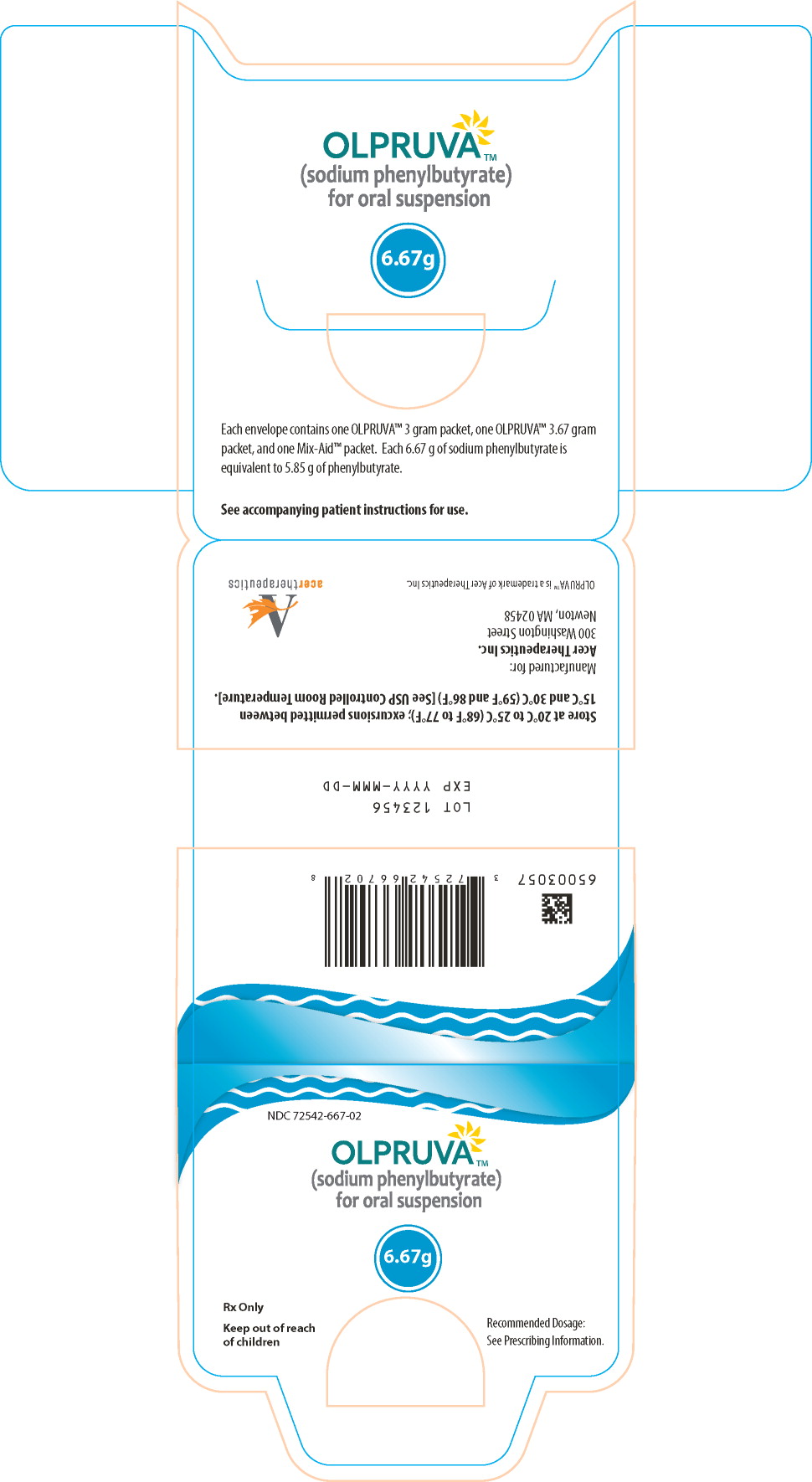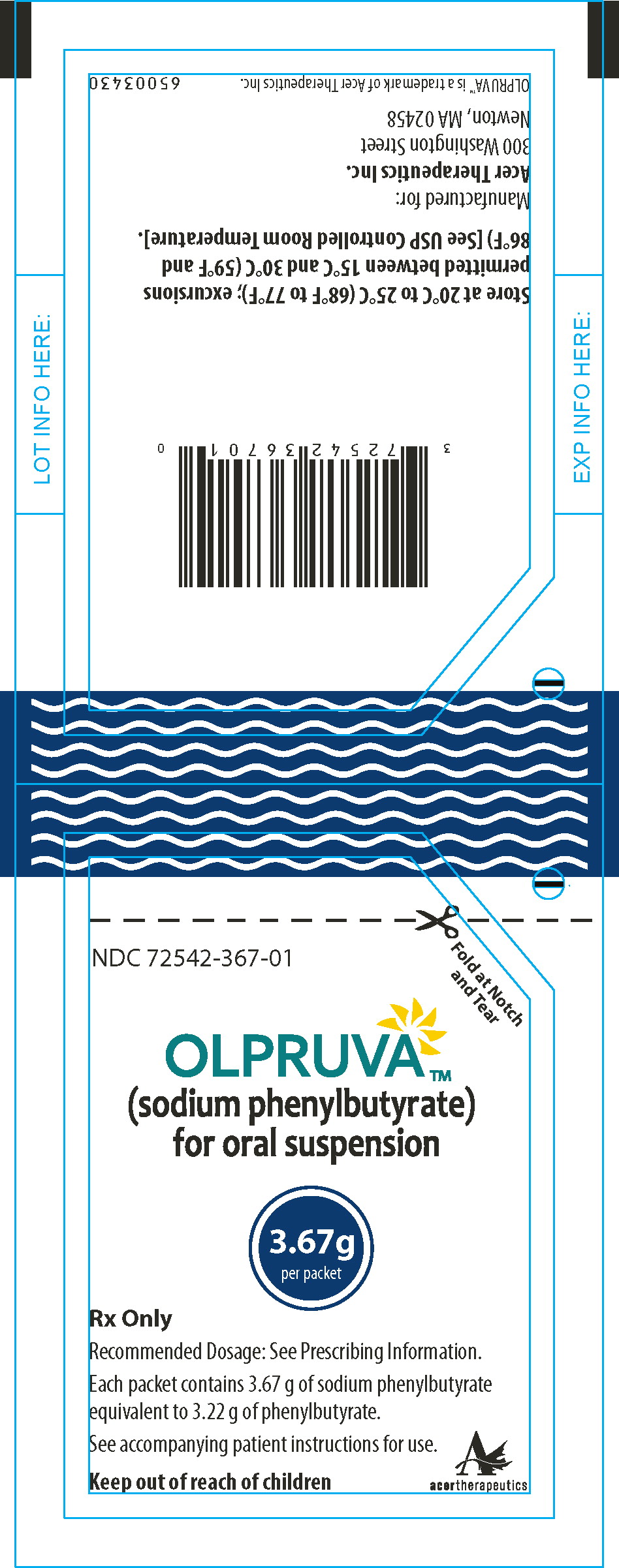 DRUG LABEL: OLPRUVA
NDC: 72542-200 | Form: KIT | Route: ORAL
Manufacturer: Acer Therapeutics Inc.
Category: prescription | Type: HUMAN PRESCRIPTION DRUG LABEL
Date: 20241218

ACTIVE INGREDIENTS: SODIUM PHENYLBUTYRATE 2 g/1 1
INACTIVE INGREDIENTS: POLYETHYLENE GLYCOL 6000; SILICON DIOXIDE; MICROCRYSTALLINE CELLULOSE; HYPROMELLOSE 2910 (5 MPA.S); TALC; DIMETHYLAMINOETHYL METHACRYLATE - BUTYL METHACRYLATE - METHYL METHACRYLATE COPOLYMER; STARCH, CORN

HIGHLIGHTS OF PRESCRIBING INFORMATION

These highlights do not include all the information needed to use OLPRUVATMsafely and effectively. See full prescribing information for OLPRUVA.
OLPRUVA (sodium phenylbutyrate) for oral suspension
Initial U.S. Approval: 1996

1 INDICATIONS AND USAGE

- OLPRUVA is a nitrogen-binding agent indicated as adjunctive therapy to standard of care, which includes dietary management, for the chronic management of adult and pediatric patients weighing 20 kg or greater and with a body surface area (BSA) of 1.2 m^2or greater, with urea cycle disorders (UCDs) involving deficiencies of carbamylphosphate synthetase (CPS), ornithine transcarbamylase (OTC), or argininosuccinic acid synthetase (AS). (1)

Limitations of Use:

OLPRUVA is not indicated for the treatment of acute hyperammonemia. (1)

2 DOSAGE AND ADMINISTRATION

- OLPRUVA treatment should be supervised by a healthcare provider experienced in the treatment of UCDs. For preparation and administration, see full prescribing information. (2.1, 2.4)
- The recommended dosage is 9.9 -13 g/m^2/day. (2.1)
- Monitor plasma ammonia levels to determine the need for dosage adjustment. (2.2)
- Monitor patients for potential neurotoxicity. (2.2)
- For patients with hepatic impairment, start at the lower end of the recommended dosing range. (2.3)

3 DOSAGE FORMS AND STRENGTHS

- For oral suspension: 2 g, 3 g, 4 g, 5 g, 6 g, and 6.67 g of sodium phenylbutyrate as pellets in packets for reconstitution. (3)

4 CONTRAINDICATIONS

None. (4)

5 WARNINGS AND PRECAUTIONS

- Neurotoxicity of Phenylacetate: Increased exposure to phenylacetate, the major metabolite of OLPRUVA, may be associated with neurotoxicity in patients with UCDs. Consider reducing the dose if neurotoxicity symptoms are present. (5.1)
- Hypokalemia: Renal excretion of phenylacetylglutamine may induce urinary loss of potassium. Monitor serum potassium during therapy and initiate appropriate treatment when necessary. (5.2)
- Conditions Associated with Edema: Calculate the total amount of sodium patients will be exposed to based on their body surface area. If a patient develops new-onset edema or worsening edema while on treatment, discontinue administration of OLPRUVA and initiate appropriate therapy. (5.3)

6 ADVERSE REACTIONS

Most common adverse reactions (incidence ≥ 3%) are menstrual dysfunction, decreased appetite, body odor and bad taste or taste aversion. (6)

To report SUSPECTED ADVERSE REACTIONS, contact Acer Therapeutics Inc. at 1-844-600-2237 or FDA at 1-800-FDA-1088 or www.fda.gov/medwatch.

7 DRUG INTERACTIONS

- Valproic Acid, Haloperidol, or Corticosteroids: May increase plasma ammonia levels; monitor ammonia levels closely. (7.1)
- Probenecid: May inhibit renal excretion of metabolites of OLPRUVA including phenylacetate and phenylacetylglutamine; monitor for potential neurotoxicity. (7.2)

FULL PRESCRIBING INFORMATION

1 INDICATIONS AND USAGE

OLPRUVA is indicated as adjunctive therapy to standard of care, which includes dietary management, for the chronic management of adult and pediatric patients weighing 20 kg or greater and with a body surface area (BSA) of 1.2 m^2or greater, with urea cycle disorders (UCDs) involving deficiencies of carbamylphosphate synthetase (CPS), ornithine transcarbamylase (OTC), or argininosuccinic acid synthetase (AS).

Limitations of Use

Episodes of acute hyperammonemia may occur in patients while on OLPRUVA. OLPRUVA is not indicated for the treatment of acute hyperammonemia, which can be a life-threatening medical emergency that requires rapid acting interventions to reduce plasma ammonia levels.

2 DOSAGE AND ADMINISTRATION

2.1 Recommended Dosage

OLPRUVA treatment should be supervised by a healthcare provider experienced in the treatment of urea cycle disorders.

The recommended dosage of OLPRUVA for patients with urea cycle disorders is 9.9 –13 g/m^2/day orally. Divide the calculated total daily dose into three to six doses. Administer as three to six divided doses and take with food.

Round each individual dose of OLPRUVA to the nearest available dosage strength. The maximum dosage is 20 grams per day. Combine OLPRUVA with dietary protein restriction and, in some cases, amino acid supplementation (e.g., essential amino acids, arginine, citrulline, and protein-free calorie supplements).

If a dose is missed, take the missed dose as soon as possible on the same day.

2.2 Dosage Administration and Monitoring

Monitor plasma ammonia levels to determine the need for dosage adjustment. Adjust the OLPRUVA dosage to maintain the plasma ammonia level within the normal range for the patient's age, taking into consideration their clinical condition (e.g., nutritional requirements, protein intake, growth parameters, etc.).

Monitor patients for potential neurotoxicity and obtain measurements of plasma phenylacetate and phenylacetylglutamine levels [ see Warnings and Precautions (5.1), Adverse Reactions (6) ]. If neurologic symptoms (e.g., vomiting, nausea, headache, somnolence, or confusion) are present in the absence of high ammonia levels or other incurrent illnesses, consider reducing the dose of OLPRUVA.

2.3 Dosage Adjustment in Patients with Hepatic Impairment

For patients with hepatic impairment, start at the lower end of the recommended dosing range and maintain patients on the lowest dose necessary to control plasma ammonia levels [ see Use in Specific Populations (8.7) ].

2.4 Preparation and Administration Instructions

For oral administration only. Do not administer via gastrostomy or nasogastric tubes.

1. Pour the entire contents of the Mix-Aid packet into approximately 4 ounces of water in a cup and stir, forming a suspension.
2. Pour the entire contents of the OLPRUVA packet(s) into the suspension and stir.
3. Drink the entire suspension within 5 minutes after stirring to minimize dissolution of coating. After 30 minutes, the suspension should be discarded.
4. Pour another 4 ounces of water into the cup and drink to make sure that any OLPRUVA remaining in the cup is consumed.

3 DOSAGE FORMS AND STRENGTHS

For oral suspension:

2 g, 3 g, 4 g, 5 g, 6 g, and 6.67 g of sodium phenylbutyrate as white to off-white pellets in packet(s) for reconstitution.

4 CONTRAINDICATIONS

None.

5 WARNINGS AND PRECAUTIONS

5.1 Neurotoxicity of Phenylacetate

Increased exposure to phenylacetate, the major metabolite of OLPRUVA, may be associated with neurotoxicity in patients with UCDs. In a study of adult cancer patients receiving intravenous phenylacetate, 250-300 mg/kg/day for 14 days, repeated at 4-week intervals, signs and symptoms of neurotoxicity, which were reversible upon discontinuation, were seen at plasma concentrations ≥ 3.5 mmol/L, and included somnolence, fatigue, and light headedness [ see Adverse Reactions (6) ]. OLPRUVA is not approved for intravenous use or for treatment of patients with cancer.

If symptoms of vomiting, nausea, headache, somnolence, or confusion are present in the absence of high ammonia levels or other intercurrent illnesses, consider reducing the dose of OLPRUVA [ see Dosage and Administration (2.2) ].

Phenylacetate caused neurotoxicity when given subcutaneously in rat pups [ see Use in Specific Populations (8.4) ].

5.2 Hypokalemia

Renal excretion of phenylacetylglutamine may induce urinary loss of potassium. Monitor serum potassium during therapy and initiate appropriate treatment when necessary.

5.3 Conditions Associated with Edema

OLPRUVA contains 124 mg (5.4 mmol) of sodium per gram of sodium phenylbutyrate (12.4% w/w) and the Mix-Aid contains 5 mg of sodium per packet, corresponding to 2.5 g (108 mmol) of sodium in the maximum daily dose of 20 g of OLPRUVA. In order to decide if administration of OLPRUVA is appropriate in patients with diseases that involve edema, such as heart failure, cirrhosis, or nephrosis, calculate the total amount of sodium patients will be exposed to based on their BSAs [ see Dosage and Administration (2.1) ]. If a patient develops new-onset edema or worsening edema while on treatment, discontinue administration of OLPRUVA and initiate appropriate therapy.

6 ADVERSE REACTIONS

The following adverse reactions associated with the use of sodium phenylbutyrate were identified in clinical studies or postmarketing reports. Because some of these reactions were reported voluntarily from a population of uncertain size, it is not always possible to reliably estimate their frequency or establish a causal relationship to drug exposure.

Most common adverse reactions (incidence ≥ 3%) are amenorrhea or menstrual dysfunction (irregular menstrual cycles), decreased appetite, body odor and bad taste or taste aversion.

Less Common Clinical Adverse Reactions

Blood and lymphatic system disorders:aplastic anemia, ecchymoses

Cardiac disorders:arrhythmia

Gastrointestinal disorders:abdominal pain, gastritis, nausea and vomiting, constipation, rectal bleeding, peptic ulcer disease, pancreatitis

Metabolism and nutrition disorders:increased weight, edema

Nervous system disorders:syncope, headache

Psychiatric disorders:depression

Renal and urinary disorders:renal tubular acidosis

Skin and subcutaneous tissue disorders:rash

Laboratory Adverse Reactions

Blood and lymphatic system disorders:anemia, leukopenia and leukocytosis, thrombocytopenia, thrombocytosis

Hepatobiliary disorders:hyperbilirubinemia, increased blood alkaline phosphatase, increased transaminases

Metabolism and nutrition disorders:acidosis, alkalosis, hyperchloremia, hypophosphatemia, hyperuricemia, hyperphosphatemia, hypernatremia, hypokalemia, hypoalbuminemia, decreased total protein

Clinical Adverse Reactions with Use of Phenylacetate

Nervous system disorders:Neurotoxicity was reported in cancer patients receiving intravenous phenylacetate, the major metabolite of OLPRUVA (OLPRUVA is not approved for intravenous use or for treatment of patients with cancer). Signs and symptoms were predominately somnolence, fatigue, and dizziness (lightheadedness); less frequently reported were headache, dysgeusia, hypoacusis, disorientation, memory impairment, and exacerbation of a pre-existing neuropathy.

7 DRUG INTERACTIONS

7.1 Potential for Other Drugs to Affect Ammonia

Corticosteroids

Use of corticosteroids may cause the breakdown of body protein and increase plasma ammonia levels.

Valproic Acid and Haloperidol

Hyperammonemia may be induced by haloperidol and by valproic acid.

Monitor plasma ammonia levels closely when corticosteroids, valproic acid, or haloperidol is used concomitantly with OLPRUVA.

7.2 Potential for Other Drugs to Affect OLPRUVA

Probenecid

Probenecid may inhibit renal excretion of the metabolites of OLPRUVA including phenylacetate and phenylacetylglutamine. Monitor patients for potential neurotoxicity and measure plasma phenylacetate and phenylacetylglutamine levels when probenecid is used concomitantly with OLPRUVA [ see Dosage and Administration (2.2) ].

8 USE IN SPECIFIC POPULATIONS

8.1 Pregnancy

Risk Summary

Available data with sodium phenylbutyrate use in pregnant women are insufficient to identify a drug associated risk of major birth defects, miscarriage or adverse maternal or fetal outcomes. Animal reproduction studies have not been conducted with sodium phenylbutyrate. Based on published animal data, phenylacetate may be neurotoxic to the developing brain (see Data).

There are serious risks to the mother and fetus associated with untreated urea cycle disorders during pregnancy which can result in serious morbidity and mortality to the mother and fetus (see Clinical Considerations).

The estimated background risk of major birth defects and miscarriage for the indicated population is unknown. All pregnancies have a background risk of birth defect, loss or other adverse outcomes. In the U.S. general population, the estimated background risk of major birth defects and miscarriage in clinically recognized pregnancies is 2% to 4% and 15% to 20%, respectively.

Clinical Considerations

Disease-Associated Maternal and/or Embryo/Fetal Risk

Pregnancy is a time of increased metabolic demand which increases the risk for hyperammonemic episodes when metabolic demands are not met. Hyperammonemic episodes in pregnancy are associated with impaired cognition in the mother and an increased risk of maternal and fetal death.

Data

Animal Data

In rats, intrauterine exposure to phenylacetate produced lesions in the neonatal brain in layer 5 of the cortical pyramidal cells; dendritic spines were longer and thinner than normal and reduced in number.

8.2 Lactation

Risk Summary

There are no data on the presence of sodium phenylbutyrate and its metabolite in either human or animal milk, the effects on the breastfed infant, or the effects on milk production. The developmental and health benefits of breastfeeding should be considered along with the mother's clinical need for OLPRUVA and any potential adverse effects on the breastfed infant from OLPRUVA or from the underlying maternal condition.

8.4 Pediatric Use

The safety and effectiveness of OLPRUVA have been established as adjunctive therapy to the standard of care, which includes dietary management, in the chronic management of pediatric patients weighing 20 kg or greater and with a body surface area 1.2 m^2or greater, with urea cycle disorders (UCDs) involving deficiencies of carbamylphosphate synthetase (CPS), ornithine transcarbamylase (OTC), or argininosuccinic acid synthetase (AS).

OLPRUVA is not indicated for the treatment of acute hyperammonemia which can be a life-threatening medical emergency that requires rapid acting interventions to reduce plasma ammonia levels.

The sodium content of OLPRUVA has the potential to cause new-onset edema or worsening edema from salt and water retention, particularly in patients with underlying predisposing conditions [ see Warnings and Precautions (5.3) ].

OLPRUVA is not approved in pediatric patients weighing less than 20 kg or in pediatric patients weighing 20 kg or greater with a BSA of less than 1.2 m^2.

Neurotoxicity has been observed in juvenile animals with phenylacetate exposure [ see Warnings and Precautions (5.1) ].

Juvenile Animal Toxicity Data

When given subcutaneously to neonatal rats, 190-474 mg/kg phenylacetate caused decreased proliferation and increased loss of neurons, and it reduced CNS myelin. Cerebral synapse maturation was retarded, and the number of functioning nerve terminals in the cerebrum was reduced, which resulted in impaired brain growth.

8.5 Geriatric Use

Clinical studies of OLPRUVA did not include sufficient numbers of subjects aged 65 and over to determine whether they respond differently from younger subjects. Other reported clinical experience has not identified differences in responses between the elderly and younger patients. In general, dose selection for an elderly patient should be cautious, usually starting at the low end of the dosing range, reflecting the greater frequency of decreased hepatic, renal, or cardiac function and of concomitant disease or other drug therapy.

8.6 Renal Impairment

No studies with OLPRUVA were conducted in subjects with renal impairment. Monitor plasma ammonia levels when starting patients with impaired renal function on OLPRUVA [ see Clinical Pharmacology (12) ].

8.7 Hepatic Impairment

No studies with OLPRUVA were conducted in subjects with hepatic impairment. Start at the lower end of the recommended dosing range and maintain patients with hepatic impairment on the lowest dose necessary to control plasma ammonia levels [ see Clinical Pharmacology (12) , Dosage and Administration (2.3) ].

10 OVERDOSAGE

Overdoses of OLPRUVA exceeding ten-fold the maximum recommended dosage may produce emesis, CNS depression, metabolic acidosis with or without respiratory alkalosis, hypernatremia, hypokalemia, and hypophosphatemia. Symptoms of overdose overlap with those of acute hyperammonemia. If overdose occurs, discontinue OLPRUVA, monitor plasma phenylacetate and ammonia levels closely, and institute appropriate emergency management, which may include hemodialysis, continuous veno-venous hemofiltration (CVVH) or extracorporeal membrane oxygenation (ECMO).

11 DESCRIPTION

OLPRUVA (sodium phenylbutyrate) for oral suspension is a nitrogen binding agent. Sodium phenylbutyrate is a white to yellowish-white powder. It is freely soluble in water and in methanol, and practically insoluble in acetone and diethyl ether. It is known chemically as sodium 4-phenylbutyrate with a molecular weight of 186.19 and molecular formula C10H11NaO2.

Structural Formula:

OLPRUVA is supplied in dosage envelopes containing 2 g (equivalent to 1.75 g phenylbutyrate), 3 g (equivalent to 2.63 g phenylbutyrate), 4 g (equivalent to 3.51 g phenylbutyrate), 5 g (equivalent to 4.38 g phenylbutyrate), 6 g (equivalent to 5.26 g phenylbutyrate), and 6.67 g (equivalent to 5.85 g phenylbutyrate) of sodium phenylbutyrate in one or two packets. OLPRUVA is a polymer coated formulation which contains the following inactive ingredients: amino methacrylate copolymer, hypromellose, microcrystalline cellulose, polyethylene glycol 6000, silicon dioxide, and talc.

12 CLINICAL PHARMACOLOGY

12.1 Mechanism of Action

Sodium phenylbutyrate is a pro-drug and is metabolized to phenylacetate. Phenylacetate is a metabolically active compound that conjugates with glutamine via acetylation to form phenylacetylglutamine. Phenylacetylglutamine is excreted by the kidneys, hence providing an alternate vehicle for waste nitrogen excretion.

12.2 Pharmacodynamics

In patients with urea cycle disorders, sodium phenylbutyrate decreased elevated plasma ammonia and glutamine levels.

12.3 Pharmacokinetics

The pharmacokinetics of phenylbutyrate and its metabolite phenylacetate were characterized in healthy adult subjects following a single oral administration of OLPRUVA (5 g of sodium phenylbutyrate) with suspension agent under fasted and fed conditions.

Absorption

The pharmacokinetic parameters for the maximum plasma concentration (Cmax) and area under the plasma concentration-time curve (AUC) of phenylbutyrate and phenylacetate under fasted conditions are summarized in Table 1.

Table 1 Cmaxand AUC of Phenylbutyrate and Phenylacetate Following a Single Oral Dose Administration of OLPRUVA (5 g) in Healthy Subjects Under Fasted Conditions
PK Parameters | Phenylbutyrate Results (Mean ± SD) | Phenylacetate Results (Mean ± SD)
Cmax(μg/mL) | 229 ± 48 | 39 ± 14
AUCinf(hr•μg/mL) | 510 ± 129 | 183 ± 76

Effect of Food

Compared to those under fasted conditions, phenylbutyrate Cmaxwas decreased by 50% and AUCinfdecreased by 39% when OLPRUVA was administered with a high-fat meal (total 980 calories with 55% fat). For the metabolite phenylacetate, Cmaxdecreased by 32% and AUCinfdecreased by 29% with a high-fat meal compared to fasted conditions.

Distribution

The apparent volume of distribution of phenylbutyrate was 7.2 L under fasted conditions.

Elimination

The mean half-life of phenylbutyrate was 0.5 hours under fasted conditions. The mean half-life of phenylacetate was 1.2 hours under fasted conditions.

Metabolism

Following oral administration, sodium phenylbutyrate is metabolized by β-oxidation into phenylacetate which is converted to its coenzyme A ester, phenylacetyl-coenzyme A and further conjugated with glutamine to form phenylacetylglutamine. Phenylacetylglutamine is excreted by the kidneys. The major sites for metabolism of sodium phenylbutyrate are the liver and kidneys. Phenylacetate is also hydrolyzed by esterases in liver and blood.

Excretion

Approximately 80-100% of sodium phenylbutyrate is excreted by the kidneys within 24 hours as phenylacetylglutamine. For each gram of sodium phenylbutyrate administered, it is estimated that between 0.12-0.15 grams of phenylacetylglutamine nitrogen are produced.

Specific Populations

Patients with Renal Impairment or Hepatic Impairment

OLPRUVA has not been studied in patients with renal impairment or in patients with hepatic impairment.

Drug Interaction Studies

In vitro or clinical studies with OLPRUVA for determination of potential drug-drug interaction have not been conducted.

13 NONCLINICAL TOXICOLOGY

13.1 Carcinogenesis, Mutagenesis, Impairment of Fertility

Carcinogenicity, mutagenicity, and fertility studies of sodium phenylbutyrate have not been conducted.

16 HOW SUPPLIED/STORAGE AND HANDLING

OLPRUVA (sodium phenylbutyrate) for oral suspension is available in dosage strengths of 2 g, 3 g, 4 g, 5 g, 6 g, and 6.67 g of sodium phenylbutyrate as white to off-white pellets. Each dose is packaged in a dosage envelope containing one or two packets of sodium phenylbutyrate for oral suspension and a suspending agent packet (labeled as Mix-Aid). A 30-day supply of OLPRUVA is provided in a kit containing 90 dosage envelopes.

Table 2 OLPRUVA Available Dosage Strengths
Dosage Strength | OLPRUVA packet(s) in each envelope | Envelope NDC | Kit NDC
2 g | one 2 g packet (NDC 72542-002-01) | 72542-200-02 | 72542-200-09
3 g | one 3 g packet (NDC 72542-003-01) | 72542-300-02 | 72542-300-09
4 g | two 2 g packets | 72542-400-02 | 72542-400-18
5 g | one 2 g packet and one 3 g packet | 72542-500-02 | 72542-500-18
6 g | two 3 g packets | 72542-600-02 | 72542-600-18
6.67 g | one 3 g packet and one 3.67 g packet (NDC 72542-367-01) | 72542-667-02 | 72542-667-18

Store OLPRUVA at 20°C to 25°C (68°F to 77°F); excursions permitted between 15°C and 30°C (59°F and 86°F) [see USP Controlled Room Temperature].

17 PATIENT COUNSELING INFORMATION

Advise the patient to read the FDA-approved patient labeling (Patient Informationand Instructions for Use).

Neurotoxicity

Advise the patient or caregiver that neurotoxicity may occur during OLPRUVA treatment. Inform the patient or caregiver of the signs and symptoms of this risk and to contact the healthcare provider immediately if signs and symptoms occur [ see Warnings and Precautions (5.1) ].

Preparation and Administration

Inform the patient or caregiver that the OLPRUVA packet(s) must be mixed with the prepared Mix-Aid suspension and to drink the entire suspension within 5 minutes after stirring to minimize dissolution of coating. After 30 minutes, the suspension should be discarded [ see Dosage and Administration (2.3) ].

Inform the patient or caregiver that if a dose is missed, take the missed dose as soon as possible on the same day [ see Dosage and Administration (2.1) ].

Manufactured for:
Acer Therapeutics Inc.
300 Washington St.
Newton, MA 02458
For more information call Acer Therapeutics Inc. at 1-844-600-2237.
© 2022 Acer Therapeutics Inc. All rights reserved.

65003012

PATIENT INFORMATION
OLPRUVA™ (ol proo vah)
(sodium phenylbutyrate)
for oral suspension

What is OLPRUVA?

- OLPRUVA is a prescription medicine used along with certain therapy, including changes in diet, for the long-term management of adults and children weighing 44 pounds (20 kg) or greater and with a body surface area (BSA) of 1.2 m^2or greater, with urea cycle disorders (UCDs), involving deficiencies of carbamylphosphate synthetase (CPS), ornithine transcarbamylase (OTC) or argininosuccinic acid synthetase (AS).
- Episodes of rapid increase of ammonia in the blood (acute hyperammonemia) may happen in people during treatment with OLPRUVA. OLPRUVA is not for the treatment of acute hyperammonemia, which can be life-threatening and requires emergency medical treatment.
- OLPRUVA is not approved in children weighing less than 44 pounds (20 kg) or in children weighing 44 pounds (20 kg) or greater with a BSA of less than 1.2 m^2.

Before taking OLPRUVA, tell your or your child's healthcare provider about all of your medical conditions, including if you:

- have heart problems
- have kidney or liver problems
- are pregnant or plan to become pregnant. It is not known if OLPRUVA will harm your unborn baby.
- are breastfeeding or plan to breastfeed. It is not known if OLPRUVA passes into breastmilk. Talk to your healthcare provider about the best way to feed your baby during treatment with OLPRUVA.

Tell your healthcare provider about all the medicines you or your child take, including prescription and over-the-counter medicines, vitamins, and herbal supplements.
Certain medicines may increase the level of ammonia in your blood or cause serious side effects when taken during treatment with OLPRUVA. Especially tell your healthcare provider if you or your child take:

- corticosteroids
- valproic acid
- haloperidol
- probenecid

Know the medicines you take. Keep a list of them to show your or your child's healthcare provider and pharmacist when you get a new medicine.

How should I or my child take OLPRUVA?
Read the detailed Instructions for Use that comes with OLPRUVA for information about the right way to prepare and take a dose of OLPRUVA.

- Take OLPRUVA exactly as prescribed by your healthcare provider.
- Your healthcare provider may change your dose if needed. Do not change your dose unless your healthcare provider tells you to.
- Your healthcare provider will prescribe OLPRUVA based on your or your child's weight.
- Take your OLPRUVA dose with food.
- If you miss a dose of OLPRUVA, take it as soon as possible that same day.
- Do notgive or take OLPRUVA through a gastrostomy or nasogastric tube.
- If you take too much OLPRUVA, call your healthcare provider or go to the nearest hospital emergency room right away.

What are the possible side effects of OLPRUVA?
OLPRUVA can cause serious side effects, including:

- Nervous system problems (neurotoxicity).Call your healthcare provider right away if you or your child get any of the following symptoms during treatment with OLPRUVA:

- sleepiness
- tiredness
- lightheadedness
- vomiting

- nausea
- headache
- confusion

- Low potassium levels in your blood (hypokalemia).Your healthcare provider will monitor your blood potassium levels during treatment with OLPRUVA and treat if needed.
- Conditions related to swelling (edema).OLPRUVA contains salt (sodium), which can cause swelling from salt and water retention. Your healthcare provider will decide if OLPRUVA is right for you if you have certain medical conditions that cause edema, such as heart failure, liver problems or kidney problems.

The most common side effects of OLPRUVA include:

- absent or irregular menstrual periods
- decreased appetite

- body odor
- bad taste or avoiding foods that you ate prior to getting sick (taste aversion)

Your healthcare provider may do certain blood tests to check you or your child for side effects during treatment with OLPRUVA.
These are not all of the possible side effects of OLPRUVA. Call your doctor for medical advice about side effects. You may report side effects to FDA at 1-800-FDA-1088.

How should I store OLPRUVA?

- Store OLPRUVA at room temperature between 68°F and 77°F (20°C and 25°C).
- Keep OLPRUVA and all medicines out of the reach of children.

General information about the safe and effective use of OLPRUVA.
Medicines are sometimes prescribed for purposes other than those listed in a Patient Information leaflet. Do not use OLPRUVA for a condition for which it was not prescribed. Do not give OLPRUVA to other people, even if they have the same symptoms that you have. It may harm them. You can ask your pharmacist or healthcare provider for information about OLPRUVA that is written for health professionals.

What are the ingredients in OLPRUVA?
Active ingredient: sodium phenylbutyrate
Inactive ingredients: amino methacrylate copolymer, hypromellose, microcrystalline cellulose, polyethylene glycol 6000, silicon dioxide, and talc.
Manufactured for:
Acer Therapeutics Inc.
300 Washington St.
Newton, MA 02458
For more information, go to www.OLPRUVA.com or call Acer Therapeutics Inc. at 1-844-600-2237.
© 2022 Acer Therapeutics Inc. All rights reserved.

This Patient Information has been approved by the U.S. Food and Drug Administration.

Issued: 12/2022

INSTRUCTIONS FOR USE
OLPRUVA™ (ol proo vah)
(sodium phenylbutyrate)
for oral suspension

Read this Instructions for Use before taking OLPRUVA oral suspension and each time you get a refill. There may be new information. This Instructions for Use does not take the place of talking to your healthcare provider about your medical condition or treatment. Talk to your healthcare provider or pharmacist if you have any questions about how to take a dose of OLPRUVA.

This Instructions for Use contains information on how to prepare and take 1 dose of OLPRUVA.

Supplies needed to take 1 dose of OLPRUVA as prescribed:

- One dosage envelope containing OLPRUVA and Mix-Aid packets. The contents of 1 envelope equals 1 full dose.
- An open drinking cup
- A spoon
- Water

Step 1:Get an open drinking cup and spoon (See Figure A).

Step 2:Add about 4 ounces of water to an open drinking cup (See Figure B).

Step 3:Remove 1 dosage envelope from the kit (See Figure C).
Note:Each kit is divided into 30 individual sections. Each section contains 3 dosage envelopes for a total of 90 dosage envelopes.

Step 4:Open the dosage envelope and remove all packets (1 packet of Mix-Aid and 1 or 2 packets of OLPRUVA) (See Figure D).
Note:All packets in the dosage envelope must be used for 1 full dose.

Step 5:To open the Mix-Aid packet, tear or cut with scissors, straight across from the notch (See Figures E and F).

Step 6:Add the full contents of the Mix-Aid packet to the water (in the open drinking cup) and stir with the spoon for at least 30 seconds (See Figure G).
Note:The contents will not dissolve but will make the water thicker so that OLPRUVA does not sink to the bottom of the cup.
Do not drink yet.

Step 7:To open the OLPRUVA packet(s), fold at the notch and tear or cut with scissors. Add the full contents of the OLPRUVA packet(s) to the open drinking cup containing the mixture from Step 6 (the water and Mix-Aid) and stir for 15 seconds (See Figure H).
Drink the entire contents of the open drinking cup within 5 minutes to help prevent the coating from dissolving (See Figure I).
Note:The entire contents of each packet must be used for 1 full dose.

Step 8:
To make sure that you get the full dose, pour another 4 ounces of water in the open drinking cup, stir (See Figure J) and drink the entire contents (See Figure K).
OLPRUVA suspension is taken by mouth only.
Do nottake or give OLPRUVA suspension in a gastrostomy or nasogastric tube.
The mixed OLPRUVA suspension should be thrown away (discarded) after 30 minutes, if not used right away.

How should I store OLPRUVA?

- Store OLPRUVA at room temperature between 68°F and 77°F (20°C and 25°C).
- Keep OLPRUVA and all medicines out of the reach of children.

Manufactured for:
Acer Therapeutics Inc.
300 Washington St.
Newton, MA 02458
For more information, go to www.OLPRUVA.com or call Acer Therapeutics Inc. at 1-844-600-2237.
© 2022 Acer Therapeutics Inc. All rights reserved.

This Instructions for Use has been approved by the U.S. Food and Drug Administration. Issued: 12/2022

Principal Display Panel – Mix-Aid Label

Tear or Cut

Mix-Aid™

Suspending agent for use with
OLPRUVA™ (sodium phenylbutyrate)
for oral suspension

Directions:Mix full contents of packet
per patient instructions for use.

The contents of this packet will NOT
dissolve but will make the water thicker
to suspend OLPRUVA™.

NET WT. 0.11 OZ (3.1 g)

Principal Display Panel - 2 g Carton Label

NDC 72542-200-09

OLPRUVA™

(sodium phenylbutyrate)
for oral suspension

2g

Rx Only

Recommended Dosage: See Prescribing Information.

Kit contains 90 dosage envelopes. Each envelope contains one OLPRUVA™ 2 gram
packet and one Mix-Aid™ packet.

Each 2 g of sodium phenylbutyrate is equivalent to 1.75 g of phenylbutyrate.

See accompanying patient instructions for use.

Store at 20°C to 25°C (68°F to 77°F); excursions permitted
between 15°C and 30°C (59°F and 86°F) [See USP Controlled
Room Temperature].

Keep out of reach of children

acertherapeutics

Principal Display Panel - 2 g Pouch Label

Fold at Notch
and Tear

NDC 72542-002-01

OLPRUVA™

(sodium phenylbutyrate)
for oral suspension

2g
per packet

Rx Only

Recommended Dosage: See Prescribing Information.

Each packet contains 2 g of sodium phenylbutyrate
equivalent to 1.75 g of phenylbutyrate.

See accompanying patient instructions for use.

Keep out of reach of children

acertherapeutics

Store at 20°C to 25°C (68°F to 77°F); excursions permitted
between 15°C and 30°C (59°F and 86°F) [See USP Controlled
Room Temperature].

Principal Display Panel - 2 g Envelope Label

NDC 72542-200-02

OLPRUVA™

(sodium phenylbutyrate)
for oral suspension

2g

Rx Only

Keep out of reach
of children

Recommended Dosage: See Prescribing Information.

Each envelope contains one OLPRUVA™ 2 gram packet and one Mix-Aid™ packet.

Each 2 g of sodium phenylbutyrate is equivalent to 1.75 g of phenylbutyrate.

acertherapeutics

Store at 20°C to 25°C (68°F to 77°F); excursions permitted
between 15°C and 30°C (59°F and 86°F) [See USP Controlled
Room Temperature].

Principal Display Panel - 3 g Carton Label

NDC 72542-300-09

OLPRUVA™

(sodium phenylbutyrate)
for oral suspension

3g

Rx Only

Recommended Dosage: See Prescribing Information.

Kit contains 90 dosage envelopes. Each envelope contains one OLPRUVA™ 3 gram
packet and one Mix-Aid™ packet.

Each 3 g of sodium phenylbutyrate is equivalent to 2.63 g of phenylbutyrate.

See accompanying patient instructions for use.

Store at 20°C to 25°C (68°F to 77°F); excursions permitted
between 15°C and 30°C (59°F and 86°F) [See USP Controlled
Room Temperature].

Keep out of reach of children

acertherapeutics

Principal Display Panel - 3 g Pouch Label

Fold at Notch
and Tear

NDC 72542-003-01

OLPRUVA™

(sodium phenylbutyrate)
for oral suspension

3g
per packet

Rx Only

Recommended Dosage: See Prescribing Information.

Each packet contains 3 g of sodium phenylbutyrate
equivalent to 2.63 g of phenylbutyrate.

See accompanying patient instructions for use.

Keep out of reach of children

acertherapeutics

Store at 20°C to 25°C (68°F to 77°F); excursions permitted
between 15°C and 30°C (59°F and 86°F) [See USP Controlled
Room Temperature].

Principal Display Panel - 3 g Envelope Label

NDC 72542-300-02

OLPRUVA™

(sodium phenylbutyrate)
for oral suspension

3g

Rx Only

Keep out of reach
of children

Recommended Dosage: See Prescribing Information.

Each envelope contains one OLPRUVA™ 3 gram packet and one Mix-Aid™ packet.

Each 3 g of sodium phenylbutyrate is equivalent to 2.63 g of phenylbutyrate.

acertherapeutics

Store at 20°C to 25°C (68°F to 77°F); excursions permitted
between 15°C and 30°C (59°F and 86°F) [See USP Controlled
Room Temperature].

Principal Display Panel - 4 g Carton Label

NDC 72542-400-18

OLPRUVA™

(sodium phenylbutyrate)
for oral suspension

4g

Rx Only

Recommended Dosage: See Prescribing Information.

Kit contains 90 dosage envelopes. Each envelope contains two OLPRUVA™ 2 gram
packets and one Mix-Aid™ packet.

Each 4 g of sodium phenylbutyrate is equivalent to 3.51 g of phenylbutyrate.

See accompanying patient instructions for use.

Store at 20°C to 25°C (68°F to 77°F); excursions permitted
between 15°C and 30°C (59°F and 86°F) [See USP Controlled
Room Temperature].

Keep out of reach of children

acertherapeutics

Principal Display Panel - 4 g Envelope Label

NDC 72542-400-02

OLPRUVA™

(sodium phenylbutyrate)
for oral suspension

4g

Rx Only

Keep out of reach
of children

Recommended Dosage: See Prescribing Information.

Each envelope contains two OLPRUVA™ 2 gram packets and one Mix-Aid™ packet.

Each 4 g of sodium phenylbutyrate is equivalent to 3.51 g of phenylbutyrate.

acertherapeutics

Store at 20°C to 25°C (68°F to 77°F); excursions permitted
between 15°C and 30°C (59°F and 86°F) [See USP Controlled
Room Temperature].

Principal Display Panel - 5 g Carton Label

NDC 72542-500-18

OLPRUVA™

(sodium phenylbutyrate)
for oral suspension

5g

Rx Only

Recommended Dosage: See Prescribing Information.

Kit contains 90 dosage envelopes. Each envelope contains one OLPRUVA™ 2 gram
packet, one OLPRUVA™ 3 gram packet, and one Mix-Aid™ packet.

Each 5 g of sodium phenylbutyrate is equivalent to 4.38 g of phenylbutyrate.

See accompanying patient instructions for use.

Store at 20°C to 25°C (68°F to 77°F); excursions permitted
between 15°C and 30°C (59°F and 86°F) [See USP Controlled
Room Temperature].

Keep out of reach of children

acertherapeutics

Principal Display Panel - 5 g Envelope Label

NDC 72542-500-02

OLPRUVA™

(sodium phenylbutyrate)
for oral suspension

5g

Rx Only

Keep out of reach
of children

Recommended Dosage: See Prescribing Information.

Each envelope contains one OLPRUVA™ 2 gram packet, one OLPRUVA™ 3 gram

packet, and one Mix-Aid™ packet.

Each 5 g of sodium phenylbutyrate is equivalent to 4.38 g of phenylbutyrate.

acertherapeutics

Store at 20°C to 25°C (68°F to 77°F); excursions permitted
between 15°C and 30°C (59°F and 86°F) [See USP Controlled
Room Temperature].

Principal Display Panel - 6 g Carton Label

NDC 72542-600-18

OLPRUVA™

(sodium phenylbutyrate)
for oral suspension

6g

Rx Only

Recommended Dosage: See Prescribing Information.

Kit contains 90 dosage envelopes. Each envelope contains two OLPRUVA™ 3 gram
packets and one Mix-Aid™ packet.

Each 6 g of sodium phenylbutyrate is equivalent to 5.26 g of phenylbutyrate.

See accompanying patient instructions for use.

Store at 20°C to 25°C (68°F to 77°F); excursions permitted
between 15°C and 30°C (59°F and 86°F) [See USP Controlled
Room Temperature].

Keep out of reach of children

acertherapeutics

Principal Display Panel - 6 g Envelope Label

NDC 72542-600-02

OLPRUVA™

(sodium phenylbutyrate)
for oral suspension

6g

Rx Only

Keep out of reach
of children

Recommended Dosage: See Prescribing Information.

Each envelope contains two OLPRUVA™ 3 gram packets and one Mix-Aid™ packet.

Each 6 g of sodium phenylbutyrate is equivalent to 5.26 g of phenylbutyrate.

acertherapeutics

Store at 20°C to 25°C (68°F to 77°F); excursions permitted
between 15°C and 30°C (59°F and 86°F) [See USP Controlled
Room Temperature].

Principal Display Panel - 6.67 g Carton Label

NDC 72542-667-18

OLPRUVA™

(sodium phenylbutyrate)
for oral suspension

6.67g

Rx Only

Recommended Dosage: See Prescribing Information.

Kit contains 90 dosage envelopes. Each envelope contains one OLPRUVA™ 3 gram
packet, one OLPRUVA™ 3.67 gram packet, and one Mix-Aid™ packet.

Each 6.67 g of sodium phenylbutyrate is equivalent to 5.85 g of phenylbutyrate.

See accompanying patient instructions for use.

Store at 20°C to 25°C (68°F to 77°F); excursions permitted
between 15°C and 30°C (59°F and 86°F) [See USP Controlled
Room Temperature].

Keep out of reach of children

acertherapeutics

Principal Display Panel - 6.67 g Envelope Label

NDC 72542-667-02

OLPRUVA™

(sodium phenylbutyrate)
for oral suspension

6.67g

Rx Only

Keep out of reach
of children

Recommended Dosage: See Prescribing Information.

Each envelope contains one OLPRUVA™ 3 gram packet, one OLPRUVA™ 3.67 gram

packet, and one Mix-Aid™ packet.

Each 6.67 g of sodium phenylbutyrate is equivalent to 5.85 g of phenylbutyrate.

acertherapeutics

Store at 20°C to 25°C (68°F to 77°F); excursions permitted
between 15°C and 30°C (59°F and 86°F) [See USP Controlled
Room Temperature].

Principal Display Panel - 3.67 g Pouch Label

Fold at Notch
and Tear

NDC 72542-367-01

OLPRUVA™

(sodium phenylbutyrate)
for oral suspension

3.67g
per packet

Rx Only

Recommended Dosage: See Prescribing Information.

Each packet contains 3.67 g of sodium phenylbutyrate
equivalent to 3.22 g of phenylbutyrate.

See accompanying patient instructions for use.

Keep out of reach of children

acertherapeutics

Store at 20°C to 25°C (68°F to 77°F); excursions permitted
between 15°C and 30°C (59°F and 86°F) [See USP Controlled
Room Temperature].